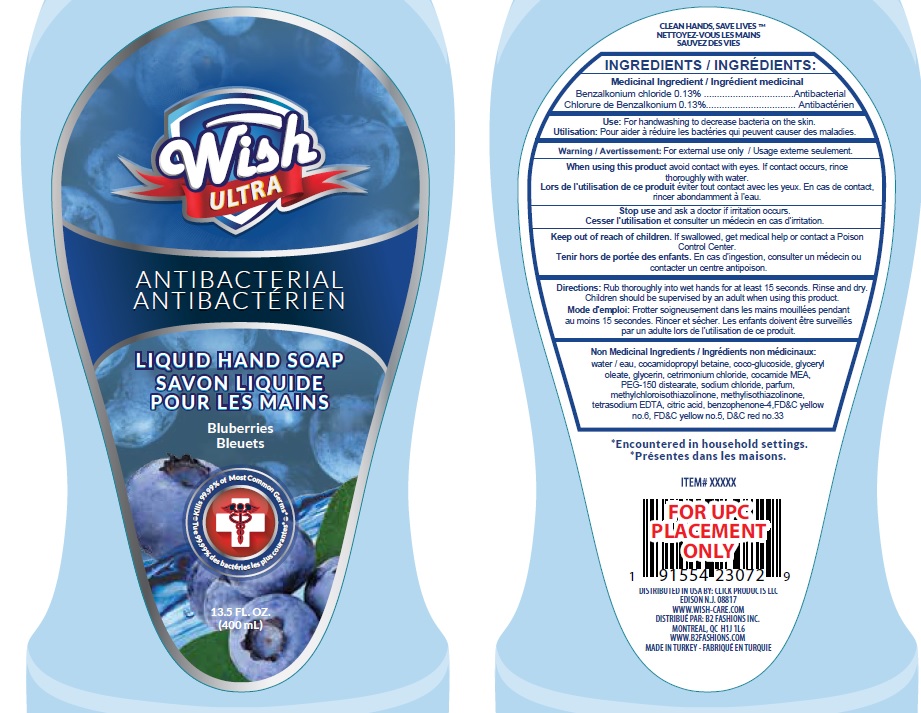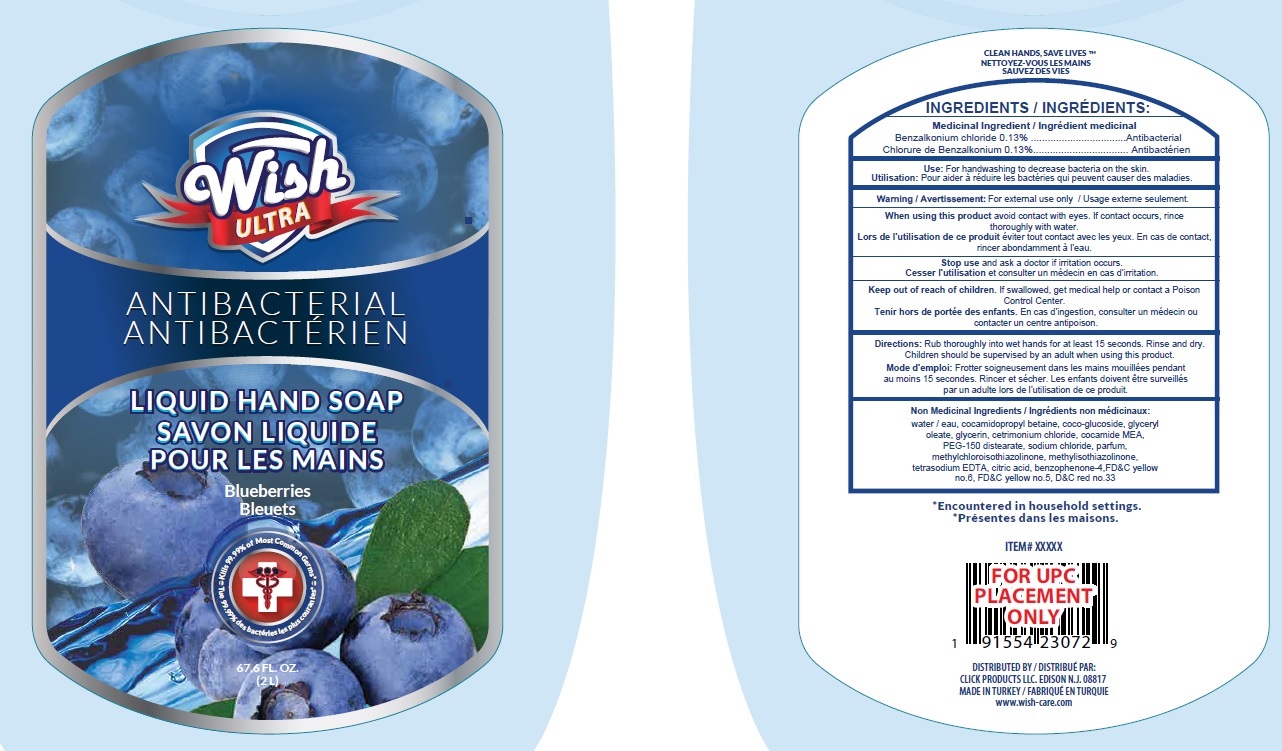 DRUG LABEL: ANTIBACTERIAL HANDWASH
NDC: 71611-042 | Form: LIQUID
Manufacturer: Click Products LLC
Category: otc | Type: HUMAN OTC DRUG LABEL
Date: 20200729

ACTIVE INGREDIENTS: BENZALKONIUM CHLORIDE 0.13 g/100 mL
INACTIVE INGREDIENTS: METHYLCHLOROISOTHIAZOLINONE; METHYLISOTHIAZOLINONE; CITRIC ACID MONOHYDRATE; SODIUM CHLORIDE; WATER; CETRIMONIUM CHLORIDE; COCAMIDOPROPYL BETAINE; COCO MONOETHANOLAMIDE; FD&C RED NO. 40; FD&C BLUE NO. 1; PEG-150 DISTEARATE; D&C RED NO. 33; GLYCERIN; EDETATE SODIUM; COCO GLUCOSIDE; SULISOBENZONE; FD&C YELLOW NO. 5; FD&C YELLOW NO. 6; BENZYL ALCOHOL

Wish ULTRA ANTIBACTERIAL LIQUID HAND SOAP

Active Ingredient

Benzalkonium Chloride 0.13%

Purpose

Antiseptic

USES

- For Handwashing to decrease bacteria on the skin

WARNING

For external use only.

WHEN USING

- avoid contact with eyes.
- If contact occurs, rinse thoroughly with water.

Stop use and ask a doctor if

- If irritation occurs.

KEEP OUT OF REACH OF CHILDREN.

If swallowed, get medical help or contact a Poison Control Center immediately.

DIRECTIONS

- Rub thoroughly into wet hands for at least 15 seconds.
- Rinse and dry children should be supervised by an adult when using this product.

Inactive Ingredients:

Water（Aqua),Cocamidopropyl Betaine, Coco-glucoside,Sodium Chloride,Fragrance, Citric Acid,Methylchloroisothiazolinone,Methylisothiazolinone,D&C Red No.33,FD&C Yellow No.6, FD&C Yellow No. 5,PEG-150 distearate,Cocamide/MEA,Benzophenone-4,Parfum,Tetrasodium EDTA.